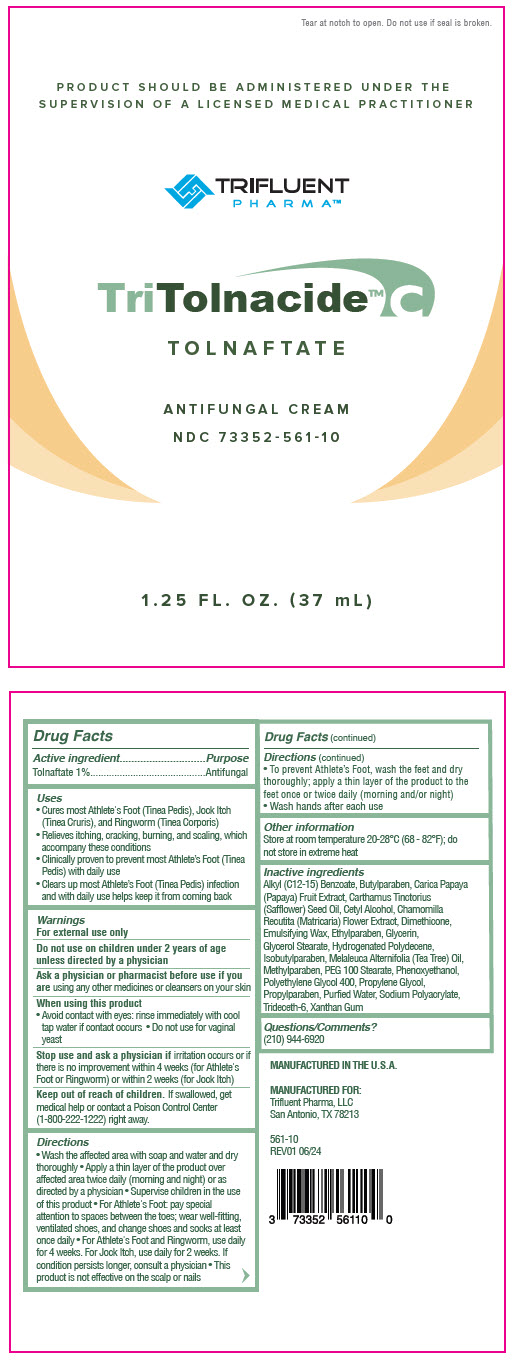 DRUG LABEL: TriTolnacide C
NDC: 73352-561 | Form: CREAM
Manufacturer: Trifluent Pharma LLC
Category: otc | Type: HUMAN OTC DRUG LABEL
Date: 20251014

ACTIVE INGREDIENTS: TOLNAFTATE 1 g/100 mL
INACTIVE INGREDIENTS: ALKYL (C12-15) BENZOATE; BUTYLPARABEN; PAPAYA; SAFFLOWER OIL; CETYL ALCOHOL; CHAMOMILE; DIMETHICONE, UNSPECIFIED; ETHYLPARABEN; GLYCERIN; GLYCERYL MONOSTEARATE; HYDROGENATED POLYDECENE TYPE I; ISOBUTYLPARABEN; TEA TREE OIL; METHYLPARABEN; PEG-100 MONOSTEARATE; PHENOXYETHANOL; POLYETHYLENE GLYCOL 400; PROPYLENE GLYCOL; PROPYLPARABEN; WATER; SODIUM POLYACRYLATE (2500000 MW); TRIDECETH-6; XANTHAN GUM

TRITOLNACIDE™ C

Drug Facts

Active ingredient

Tolnaftate 1%

Purpose

Antifungal

Uses

- Cures most Athlete's Foot (Tinea Pedis), Jock Itch (Tinea Cruris), and Ringworm (Tinea Corporis)
- Relieves itching, cracking, burning, and scaling, which accompany these conditions
- Clinically proven to prevent most Athlete's Foot (Tinea Pedis) with daily use
- Clears up most Athlete's Foot (Tinea Pedis) infection and with daily use helps keep it from coming back

Warnings

For external use only

Do not use on children under 2 years of age unless directed by a physician

ASK DOCTOR/PHARMACIST

Ask a physician or pharmacist before use if you are using any other medicines or cleansers on your skin

When using this product

- Avoid contact with eyes: rinse immediately with cool tap water if contact occurs
- Do not use for vaginal yeast

Stop use and ask a physician if irritation occurs or if there is no improvement within 4 weeks (for Athlete's Foot or Ringworm) or within 2 weeks (for Jock Itch)

Keep out of reach of children. If swallowed, get medical help or contact a Poison Control Center (1-800-222-1222) right away.

Directions

- Wash the affected area with soap and water and dry thoroughly
- Apply a thin layer of the product over affected area twice daily (morning and night) or as directed by a physician
- Supervise children in the use of this product
- For Athlete's Foot: pay special attention to spaces between the toes; wear well-fitting, ventilated shoes, and change shoes and socks at least once daily
- For Athlete's Foot and Ringworm, use daily for 4 weeks. For Jock Itch, use daily for 2 weeks. If condition persists longer, consult a physician
- This product is not effective on the scalp or nails
- To prevent Athlete's Foot, wash the feet and dry thoroughly; apply a thin layer of the product to the feet once or twice daily (morning and/or night)
- Wash hands after each use

Other information

Store at room temperature 20-28°C (68 - 82°F); do not store in extreme heat

Inactive ingredients

Alkyl (C12-15) Benzoate, Butylparaben, Carica Papaya (Papaya) Fruit Extract, Carthamus Tinctorius (Safflower) Seed Oil, Cetyl Alcohol, Chamomilla Recutita (Matricaria) Flower Extract, Dimethicone, Emulsifying Wax, Ethylparaben, Glycerin, Glycerol Stearate, Hydrogenated Polydecene, Isobutylparaben, Melaleuca Alternifolia (Tea Tree) Oil, Methylparaben, PEG 100 Stearate, Phenoxyethanol, Polyethylene Glycol 400, Propylene Glycol, Propylparaben, Purfied Water, Sodium Polyacrylate, Trideceth-6, Xanthan Gum

Questions/Comments?

(210) 944-6920

PRINCIPAL DISPLAY PANEL - 37 mL Pouch Tube Label

Tear at notch to open. Do not use if seal is broken.

PRODUCT SHOULD BE ADMINISTERED UNDER THE
SUPERVISION OF A LICENSED MEDICAL PRACTITIONER

TRIFLUENT
PHARMA™

TriTolnacide™ C

TOLNAFTATE

ANTIFUNGAL CREAM
NDC 73352-561-10

1.25 FL. OZ. (37 mL)